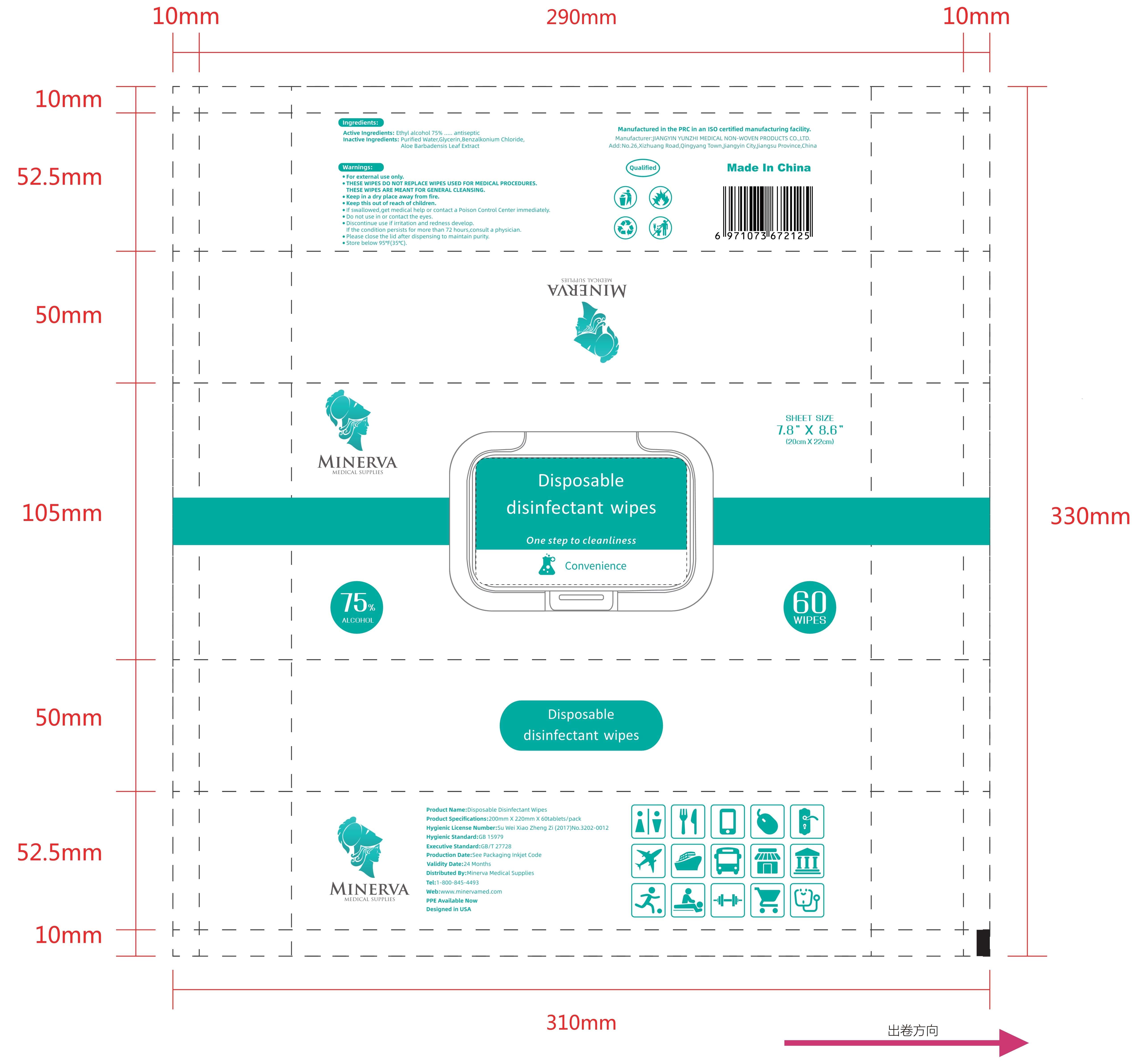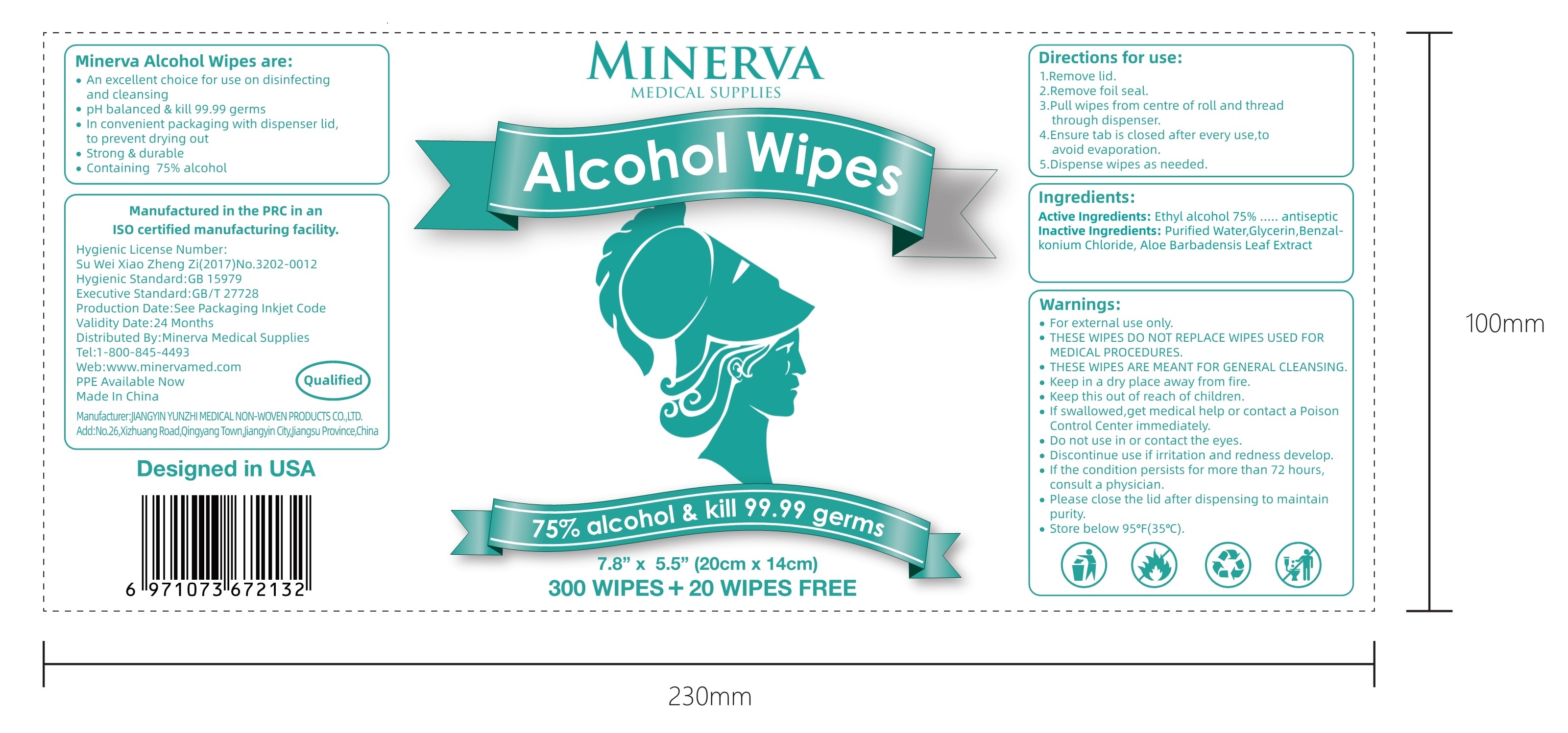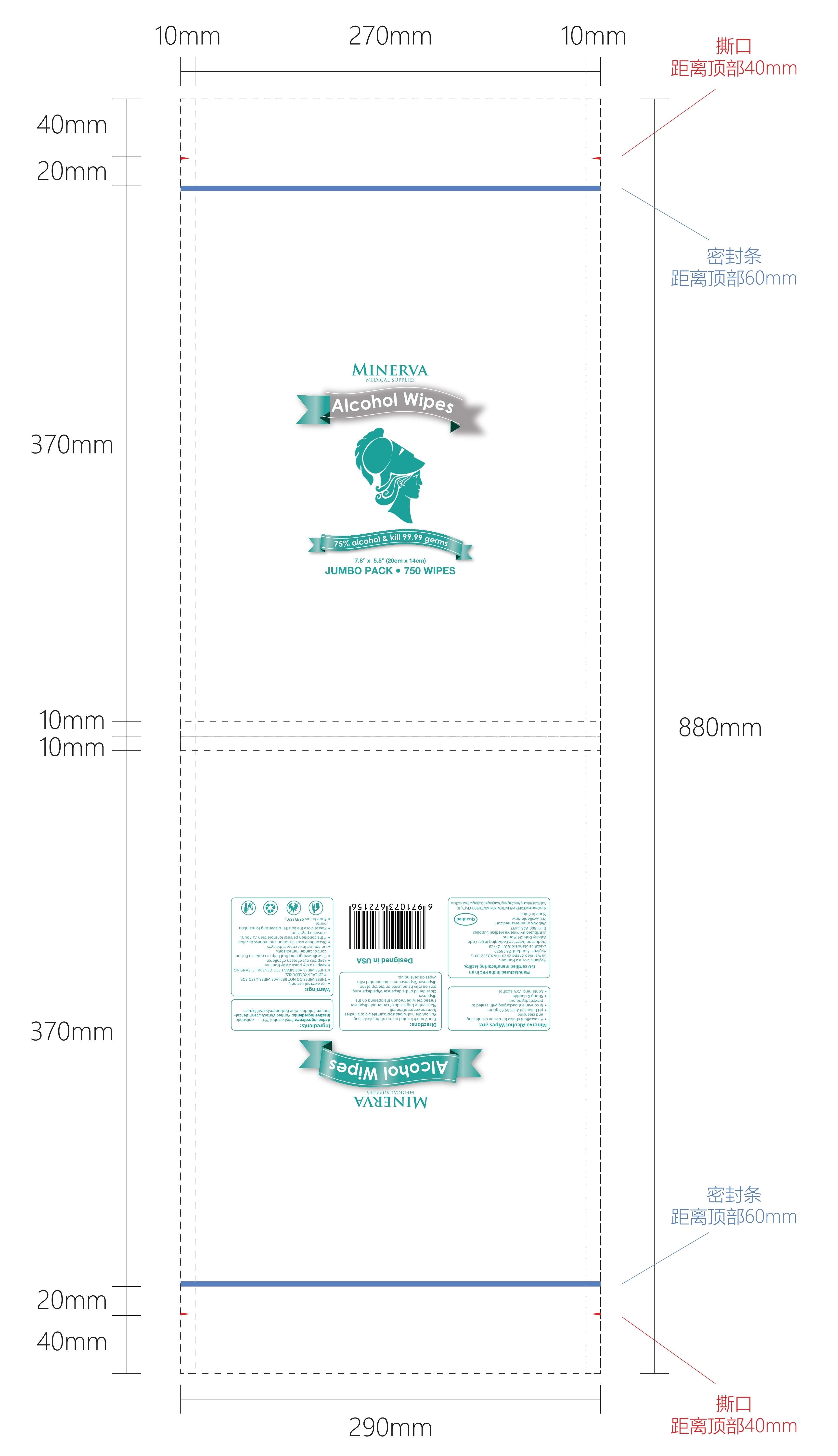 DRUG LABEL: Alcohol wipes
NDC: 80538-001 | Form: CLOTH
Manufacturer: Jiangyin Yunzhi Medical Non-woven Products Co., Ltd
Category: otc | Type: HUMAN OTC DRUG LABEL
Date: 20200926

ACTIVE INGREDIENTS: ALCOHOL 75 mL/100 1
INACTIVE INGREDIENTS: GLYCERIN; BENZALKONIUM; WATER; ALOE VERA LEAF

80538-001
Alcohol wipes

Active Ingredient(s)

Ethyl alcohol 75% ..... antiseptic

Purpose

Antiseptic, Hand Sanitizer

Use

For external use only.

THESE WIPES DO NOT REPLACE WIPES USED FOR MEDICAL PROCEDURES.
THESE WIPES ARE MEANT FOR GENERAL CLEANSING.
Keep in a dry place away from fire.

Warnings

For external use only.
THESE WIPES DO NOT REPLACE WIPES USED FOR MEDICAL PROCEDURES.
THESE WIPES ARE MEANT FOR GENERAL CLEANSING.
Keep in a dry place away from fire.

Keep this out of reach of children.
If swallowed,get medical help or contact a Poison Control Center immediately.

Do not use in or contact the eyes.
Discontinue use if irritation and redness develop.

If the condition persists for more than 72 hours, consult a physician.
Please close the lid after dispensing to maintain purity.

Store below 95°F(35°C).

Do not use

THESE WIPES DO NOT REPLACE WIPES USED FOR MEDICAL PROCEDURES.
THESE WIPES ARE MEANT FOR GENERAL CLEANSING.

Do not use in or contact the eyes.
Discontinue use if irritation and redness develop.

WHEN USING

Keep in a dry place away from fire.

Keep this out of reach of children.
If swallowed,get medical help or contact a Poison Control Center immediately.

Do not use in or contact the eyes.
Discontinue use if irritation and redness develop.

STOP USE

/

Keep this out of reach of children.
If swallowed,get medical help or contact a Poison Control Center immediately.

Directions

l.Remove lid.
2.Remove foil seal.
3.Pull wipes from centre of roll and thread through dispenser.
4.Ensure tab is closed after every use,to avoid evaporation.
5.Dispense wipes as needed.

Other information

If the condition persists for more than 72 hours, consult a physician.
Please close the lid after dispensing to maintain purity.

Store below 95°F(35°C).

Inactive ingredients

Purified Water,Glycerin,Benzalkonium Chloride, Aloe Barbadensis Leaf Extract